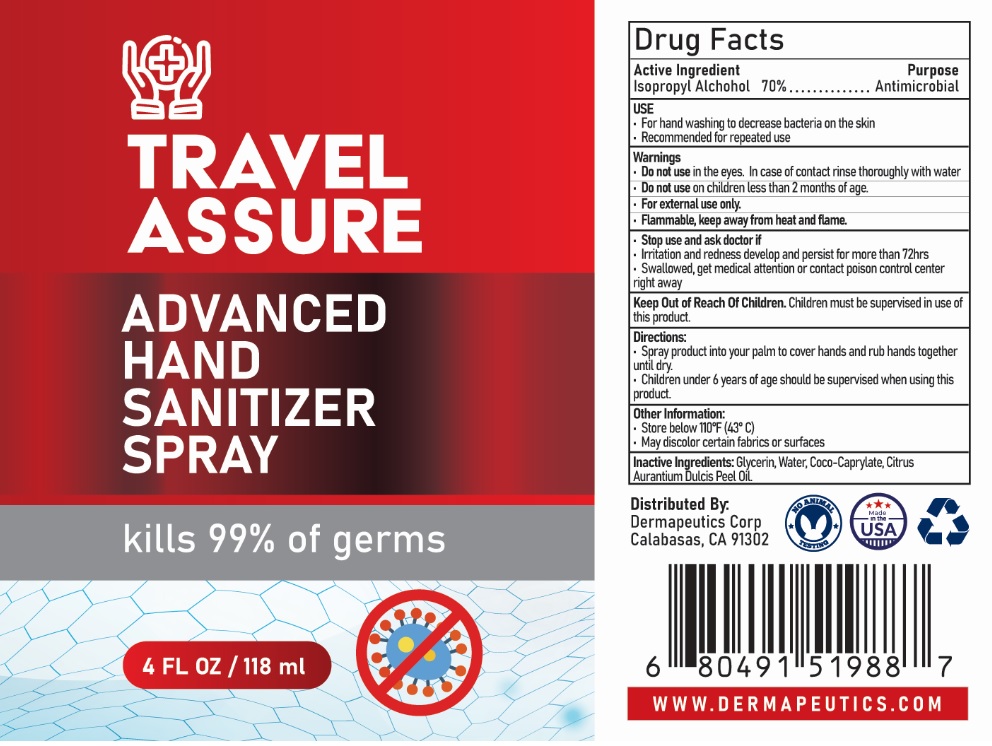 DRUG LABEL: Travel Assure Advanced Hand Sanitizer
NDC: 79416-556 | Form: SPRAY
Manufacturer: Dermapeutics
Category: otc | Type: HUMAN OTC DRUG LABEL
Date: 20200709

ACTIVE INGREDIENTS: ISOPROPYL ALCOHOL 70 mL/100 mL
INACTIVE INGREDIENTS: GLYCERIN; WATER; COCOYL CAPRYLOCAPRATE; ORANGE OIL

TRAVEL ASSURE ADVANCED HAND SANITIZER SPRAY

Active Ingredient

Isopropyl Alcohol 70%

Purpose

Antimicrobial

USE

- For hand washing to decrease bacteria on the skin
- Recommended for repeated use

Warnings

- Do not use in the eyes. In case of contact rinse thoroughly with water
- Do not use on children less than 2 months of age.
- For external use only.
- Flammable, keep away from heat and flame.
- Stop use and ask doctor if
- Irritation and redness develop and persist for more than 72hrs
- Swallowed, get medical attention or contact poison control center right away.

Keep Out of Reach Of Children. Children must be supervised in use of this product.

Directions:

- Spray product into palm to cover hands and rub hands together until dry.
- Children under 6 years of age should be supervised when using this product.

Other Information:

- Store below 110°F (43°C)
- May discolor certain fabrics or surfaces

INACTIVE INGREDIENT

Inactive Ingredients: Glycerin, Water, Coco-Caprylate, Citrs Aurantium Dulcis Peel Oil.

kills 99.9% of germs

Distributed By:

Dermapeutics Corp

Calabasas, CA 91302

NO ANIMAL TESTING

Made in the USA

WWW.DERMAPEUTICS.COM